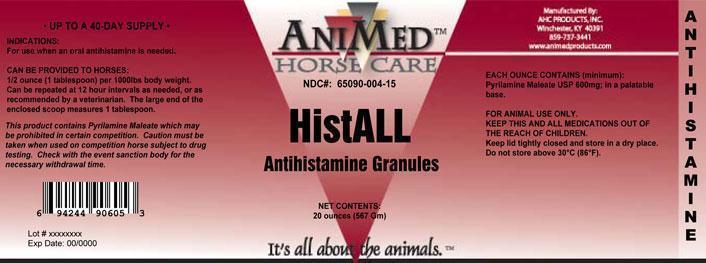 DRUG LABEL: HistALL
NDC: 65090-004 | Form: GRANULE
Manufacturer: AHC Products Inc
Category: animal | Type: OTC ANIMAL DRUG LABEL
Date: 20200131

ACTIVE INGREDIENTS: Pyrilamine Maleate 600 mg/28.3 g
INACTIVE INGREDIENTS: SACCHAROMYCES CEREVISIAE; Dextrose; STARCH, CORN; Peppermint 

HistALL

INDICATIONS AND USAGE

For use when an oral antihistamine is needed.
Can be provided to horse: 1/2 ounce (1 tablespoon) per 1000lbs body weight. Can be repeated at 12 hour intervals as needed, or as recommended by a veterinarian. The large end of the enclosed scoop measures 1 tablespoon.
This product contains Pyrilamine Maleate which may be prohibited in certain competition. Caution must be taken when used on competition horse subject to drug testing. Check with the event sanction body for the necessary withdrawal time.

ACTIVE INGREDIENT

EACH OUNCE CONTAINS (minimum): Pyrilamine Maleat USP 600mg, in a palatable base.

WARNINGS

FOR ANIMAL USE ONLY.
KEEP THIS AND ALL MEDICATIONS OUT OF THE REACH OF CHILDREN.
Keep lid tightly closed and store in a dry place Do not store above 30 C (86 F).

PACKAGE LABEL

NDC#: 65090-004-15
HistALL
Antihistamine Granules
Net Contents: 20 ounces (567 Gm)